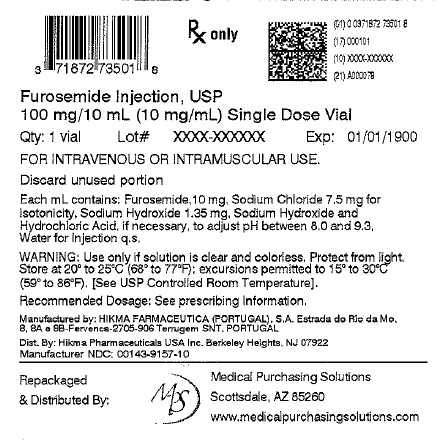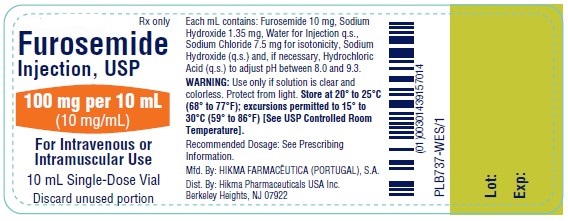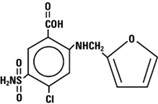 DRUG LABEL: Furosemide
NDC: 71872-7350 | Form: INJECTION
Manufacturer: Medical Purchasing Solutions, LLC.
Category: prescription | Type: HUMAN PRESCRIPTION DRUG LABEL
Date: 20251027

ACTIVE INGREDIENTS: FUROSEMIDE 10 mg/1 mL
INACTIVE INGREDIENTS: SODIUM CHLORIDE; WATER; SODIUM HYDROXIDE; HYDROCHLORIC ACID

HIGHLIGHTS OF PRESCRIBING INFORMATION

These highlights do not include all the information needed to use FUROSEMIDE INJECTION safely and effectively. See full prescribing information for FUROSEMIDE INJECTION.
FUROSEMIDE injection, for intravenous or intramuscular use
Initial U.S. Approval: 1982

1 INDICATIONS AND USAGE

Furosemide injection is a loop diuretic indicated for:

- The treatment of edema associated with heart failure, cirrhosis of the liver, and renal disease (1.1)
- Acute pulmonary edema as adjunctive therapy (1.2)

2 DOSAGE AND ADMINISTRATION

Edema:

- Initial dose is 20 mg to 40 mg once given intramuscularly or intravenously. The intravenous dose should be administered slowly over 1 minute to 2 minutes (2.2)
- If needed, a second dose may be administered 2 hours after the first dose (2.2)
- May be administered as a continuous intravenous infusion at a rate not greater then 4 mg/min (2.2)
  Acute Pulmonary Edema:
- Initial dose is 40 mg injected slowly intravenously over 1 minute to 2 minutes (2.2)
- If needed, a second dose is 80 mg injected intravenously slowly over 1 minute to 2 minutes may be given after 1 hour (2.2)
  Pediatric Dosage:
- The initial dose in pediatric patients is 1 mg/kg body weight once given slowly intramuscularly or intravenously. If needed, dosage may be increased by 1 mg/kg not sooner than 2 hours after the previous dose, until the desired diuretic effect has been obtained. Doses greater than 6 mg/kg body weight are not recommended (2.3)

3 DOSAGE FORMS AND STRENGTHS

Injection: Furosemide Injection, USP is supplied as a sterile, colorless solution as

- 20 mg/2 mL (10 mg/mL) in a single-dose vial (3)
- 40 mg/4 mL (10 mg/mL) in a single-dose vial (3)
- 100 mg/10 mL (10 mg/mL) in a single-dose vial (3)
- 500 mg/50 mL (10 mg/mL) in a single-dose vial with hanger (3)
- 1,000 mg/100 mL (10 mg/mL) in a single-dose vial with hanger (3)

4 CONTRAINDICATIONS

- Anuria (4)
- Hypersensitivity to furosemide (4)

5 WARNINGS AND PRECAUTIONS

- Fluid, Electrolyte, and Metabolic Abnormalities: Monitor serum electrolytes, CO2, BUN, creatinine, glucose, and uric acid (5.1)
- Worsening Renal Function: Monitor for dehydration and azotemia. (5.2)
- Ototoxicity:Avoid rapid injection and higher than recommended doses. (5.3, 7.1)
- Acute Urinary Retention: Monitor patients with symptoms of urinary retention. (5.4)

6 ADVERSE REACTIONS

Most common adverse reactions are related to fluid and electrolyte imbalance (6)

To report SUSPECTED ADVERSE REACTIONS, contact Hikma Pharmaceuticals USA Inc. at 1-877-845-0689 or FDA at 1-800-FDA-1088 orwww.fda.gov/medwatch.

7 DRUG INTERACTIONS

- Aminoglycoside antibiotics: Increased potential ototoxicity of the antibiotics. Avoid combination (7.1)
- Ethacrynic acid: Risk of ototoxicity. Avoid combination (7.1)
- Salicylates: Risk of salicylate toxicity (7.1)
- Cisplatin and nephrotoxic drugs: Risk of ototoxicity and nephrotoxicity (7.1)
- Lithium: Risk of lithium toxicity (7.1)
- Renin-angiotensin inhibitors: Increased risk of hypotension and renal failure.(7.1)
- Adrenergic blocking drugs: Risk of potentiation (7.1)
- Drugs undergoing renal tubular secretion: Risk of toxicity potentiation (7.1)

8 USE IN SPECIFIC POPULATIONS

See 17 for Patient Counseling Information

FULL PRESCRIBING INFORMATION

1 INDICATIONS AND USAGE

1.1 Edema

Furosemide injection is indicated in adults and pediatric patients for the treatment of edema associated with heart failure, cirrhosis of the liver, and renal disease, including the nephrotic syndrome.

1.2 Acute Pulmonary Edema

Furosemide injection is indicated as adjunctive therapy in acute pulmonary edema.

2 DOSAGE AND ADMINISTRATION

2.1 General Considerations

Inspect Furosemide injection visually for particulate matter and discoloration before administration. Discard unused portion.

2.2 Recommended Dosage for Adults

Edema

Individualize therapy according to patient response.

The usual initial dose of furosemide is 20 mg to 40 mg given as a single-dose, injected intramuscularly or intravenously. Give the intravenous dose slowly (over 1 minute to 2 minutes). If needed, administer another dose in the same manner 2 hours later or increase the dose. The dose may be raised by 20 mg and administered not sooner than 2 hours after the previous dose until the desired diuretic effect has been obtained. Administer this individually determined single-dose once or twice daily.

Furosemide may also be administered via continuous intravenous infusion at a rate not greater than 4 mg/min.

Acute Pulmonary Edema

The usual initial dose of furosemide is 40 mg injected slowly intravenously (over 1 minute to 2 minutes). If a satisfactory response does not occur within 1 hour, increase the dose to 80 mg injected slowly intravenously (over 1 minute to 2 minutes).

2.3 Recommended Dosage for Pediatric Patients

The usual initial dose of Furosemide injection (intravenously or intramuscularly) in pediatric patients is 1 mg/kg body weight administered slowly (over 1 minute to 2 minutes). If the diuretic response to the initial dose is not satisfactory, dosage may be increased by 1 mg/kg not sooner than 2 hours after the previous dose, until the desired diuretic effect has been obtained. Doses greater than 6 mg/kg body weight are not recommended.

The maximum dose for premature infants should not exceed 1 mg/kg/day [see Use in Specific Populations (8.4)] .

3 DOSAGE FORMS AND STRENGTHS

Injection: Furosemide Injection, USP is supplied as a sterile, colorless solution as

- 20 mg/2 mL (10 mg/mL) in a single-dose vial
- 40 mg/4 mL (10 mg/mL) in a single-dose vial
- 100 mg/10 mL (10 mg/mL) in a single-dose vial
- 500 mg/50 mL (10 mg/mL) in a single-dose vial with hanger
- 1,000 mg/100 mL (10 mg/mL) in a single-dose vial with hanger

4 CONTRAINDICATIONS

- Furosemide injection is contraindicated in patients with anuria.
- Furosemide injection is contraindicated in patients with a history of hypersensitivity to furosemide.

5 WARNINGS AND PRECAUTIONS

5.1 Fluid, Electrolyte, and Metabolic Abnormalities

Furosemide may cause fluid, electrolyte, and metabolic abnormalities such as hypovolemia, hypokalemia, azotemia, hyponatremia, hypochloremic alkalosis, hypomagnesemia, hypocalcemia, hyperglycemia, or hyperuricemia, particularly in patients receiving higher doses, patients with inadequate oral electrolyte intake, and in elderly patients. Excessive diuresis may cause dehydration and blood volume reduction with circulatory collapse and possibly vascular thrombosis and embolism, particularly in elderly patients. Serum electrolytes, CO2, BUN, creatinine, glucose, and uric acid should be monitored frequently during furosemide therapy.

In patients with hepatic cirrhosis and ascites, sudden alterations of fluid and electrolyte balance may precipitate hepatic encephalopathy and coma. Treatment in such patients is best initiated in the hospital with small doses and careful monitoring of the patient's clinical status and electrolyte balance.

5.2 Worsening Renal Function

Furosemide can cause dehydration and azotemia. If increasing azotemia and oliguria occur during treatment of severe progressive renal disease, furosemide should be discontinued [see Clinical Pharmacology (12.3)] .

Furosemide use in the first year of life, especially in patients born pre-term, may precipitate nephrocalcinosis/nephrolithiasis. Therefore renal function must be monitored and renal ultrasonography performed in this age group [see Use in Specific Populations (8.4)] .

5.3 Ototoxicity

Cases of tinnitus and reversible or irreversible hearing impairment and deafness have been reported. Reports usually indicate that furosemide ototoxicity is associated with rapid injection, severe renal impairment, the use of higher than recommended doses, hypoproteinemia or concomitant therapy with aminoglycoside antibiotics, ethacrynic acid, or other ototoxic drugs. If the physician elects to use high-dose parenteral therapy, controlled intravenous infusion is advisable (for adults, an infusion rate not exceeding 4 mg furosemide per minute has been used) [see Drug Interactions (7.1)] .

Hearing loss in neonates, including premature neonates has been associated with the use of Furosemide injection [see Use in Specific Populations (8.4)].

5.4 Acute Urinary Retention

In patients with severe symptoms of urinary retention (because of bladder emptying disorders, prostatic hyperplasia, urethral narrowing), the administration of furosemide can cause acute urinary retention related to increased production and retention of urine. Thus, these patients require careful monitoring, especially during the initial stages of treatment.

6 ADVERSE REACTIONS

The following adverse reactions are described elsewhere in the labeling:

- Fluid, Electrolyte, and Metabolic Abnormalities [see Warnings and Precautions (5.1)]
- Ototoxicity [see Warnings and Precautions (5.3)]

The following adverse reactions associated with the use of furosemide were identified in clinical studies or postmarketing reports. Because some of these reactions were reported voluntarily from a population of uncertain size, it is not always possible to reliably estimate their frequency or establish a causal relationship to drug exposure.

Adverse reactions are categorized below by organ system and listed by decreasing severity.

Gastrointestinal System Reactions:pancreatitis, jaundice (intrahepatic cholestatic jaundice), increased liver enzymes, anorexia, oral and gastric irritation, cramping, diarrhea, constipation, nausea, vomiting.

Systemic Hypersensitivity Reactions:severe anaphylactic or anaphylactoid reactions (e.g., with shock), systemic vasculitis, interstitial nephritis, necrotizing angiitis.

Central Nervous System Reactions:tinnitus and hearing loss, paresthesias, vertigo, dizziness, headache, blurred vision, xanthopsia.

Hematologic Reactions:aplastic anemia, thrombocytopenia, agranulocytosis, hemolytic anemia, leukopenia, anemia, eosinophilia.

Dermatologic-Hypersensitivity Reactions:toxic epidermal necrolysis, Stevens-Johnson Syndrome, erythema multiforme, drug rash with eosinophilia and systemic symptoms, acute generalized exanthematous pustulosis, exfoliative dermatitis, bullous pemphigoid, purpura, photosensitivity, rash.

Cardiovascular Reactions:orthostatic hypotension, increase in cholesterol and triglyceride serum levels.

Other Reactions:glycosuria, muscle spasm, weakness, restlessness, urinary bladder spasm, thrombophlebitis, transient injection site pain following intramuscular injection, fever.

7 DRUG INTERACTIONS

7.1 Effects of Furosemide on Other Drugs

Drug/Substance Class or Name | Drug Interaction Effect | Recommendations
Aminoglycoside antibiotics | Furosemide may increase the ototoxic potential of aminoglycoside antibiotics, especially in the presence of impaired renal function [see Warnings and Precautions (5.3)]. | Avoid combination except in life-threatening situations.
Ethacrynic acid | Possibility of ototoxicity [see Warnings and Precautions (5.3)]. | Avoid concomitant use with ethacrynic acid.
Salicylates | May experience salicylate toxicity at lower doses because of competitive renal excretory sites. | Monitor for symptoms of salicylate toxicity.
Cisplatin | There is a risk of ototoxic effects if cisplatin and furosemide are given concomitantly [see Warnings and Precautions (5.3)].
Cisplatin and nephrotoxic drugs | Nephrotoxicity | Administer furosemide at lower doses and with positive fluid balance when used to achieve forced diuresis during cisplatin treatment. Monitor renal function.
Paralytic agents | Furosemide has a tendency to antagonize the skeletal muscle relaxing effect of tubocurarine and may potentiate the action of succinylcholine. | Monitor for skeletal muscle effect.
Lithium | Furosemide reduces lithium’s renal clearance and add a high-risk of lithium toxicity. | Avoid concomitant use with lithium.
Angiotensin converting enzyme inhibitors or angiotensin II receptor blockers | May lead to severe hypotension and deterioration in renal function, including renal failure. | Monitor for changes in blood pressure and renal function and interrupt or reduce the dosage of furosemide, angiotensin converting enzyme inhibitors, or angiotensin receptor blockers if needed.
Antihypertensive drugs | Furosemide may add to or potentiate the therapeutic effect of other antihypertensive drugs. | Monitor for changes in blood pressure and adjust the dose of other antihypertensive drugs if needed.

Adrenergic blocking drugs or peripheral adrenergic blocking drugs | Potentiation occurs. | Monitor for changes in blood pressure and adjust the dose of adrenergic blocking drugs if needed.
Norepinephrine | Furosemide may decrease arterial responsiveness (vasoconstricting effect) to norepinephrine. | Monitor blood pressure (or mean arterial pressure).
Chloral hydrate | In isolated cases, intravenous administration of furosemide within 24 hours of taking chloral hydrate may lead to flushing, sweating attacks, restlessness, nausea, increase in blood pressure, and tachycardia. | Concomitant use with chloral hydrate is not recommended.
Methotrexate and other drugs undergoing renal tubular secretion | Furosemide may decrease renal elimination of other drugs that undergo tubular secretion. High-dose treatment of furosemide may result in elevated serum levels of these drugs and may potentiate their toxicity. | Monitor serum levels of drugs undergoing renal tubular secretion and adjust the dose if needed.
Cephalosporin | Furosemide can increase the risk of cephalosporin-induced nephrotoxicity even in the setting of minor or transient renal impairment. | Monitor for changes in renal function.
Cyclosporine | Increased risk of gouty arthritis secondary to furosemide-induced hyperuricemia and cyclosporine impairment of renal urate excretion. | Monitor serum urate levels.
Thyroid hormones | High-doses (> 80 mg) of furosemide may inhibit the binding of thyroid hormones to carrier proteins and result in transient increase in free thyroid hormones, followed by an overall decrease in total thyroid hormone levels. | Monitor the total thyroid hormone levels.

7.2 Effects of Other Drugs on Furosemide

Drug/Substance Class or Name | Drug Interaction Effect | Recommendations
Phenytoin | Interferes directly with renal action of furosemide. | Monitor diuretic effects of furosemide and adjust the dose of furosemide if needed.
Methotrexate and other drugs undergoing renal tubular secretion | May reduce the effect of furosemide. High-dose treatment of methotrexate and these other drugs may result in elevated serum levels of furosemide and may potentiate the toxicity of furosemide. | Monitor for enhanced toxicity of furosemide.
Indomethacin | Coadministration of indomethacin may reduce the natriuretic and antihypertensive effects of furosemide in some patients by inhibiting prostaglandin synthesis. Indomethacin may also affect plasma renin levels, aldosterone excretion, and renin profile evaluation. | Patients receiving both indomethacin and furosemide should be observed closely to determine if the desired diuretic and/or antihypertensive effect of furosemide is achieved.

8 USE IN SPECIFIC POPULATIONS

8.1 Pregnancy

Risk Summary

Available data from published observational studies, case reports, and postmarketing reports, from decades of use, have not demonstrated a drug-associated risk of major birth defects, miscarriage, or other adverse maternal or fetal outcomes with furosemide use during pregnancy. Untreated congestive heart failure and cirrhosis of the liver can lead to adverse outcomes for the mother and the fetus (see Clinical Considerations).

In animal reproduction studies, furosemide has been shown to cause unexplained maternal deaths and abortions in rabbits when administered orally during organogenesis at 4 times a human i.v. dose of 80 mg based on body surface area (BSA) and oral bioavailability corrections, presumably secondary to volume depletion (see Data).

The estimated background risk for major birth defects and miscarriage for the indicated populations is unknown. All pregnancies have a background risk of birth defect, loss, or other adverse outcomes. In the U.S. general population, the estimated background risk of major birth defects and miscarriage in the clinically recognized pregnancies is 2 to 4% and 15 to 20%, respectively.

Clinical Considerations

Disease-Associated Maternal and/or Embryo/Fetal Risk

Pregnant women with congestive heart failure are at increased risk for pre-term birth. Stroke volume and heart rate increase during pregnancy, increasing cardiac output, especially during the first trimester. Clinical classification of heart disease may worsen with pregnancy and lead to maternal death and/or stillbirth. Closely monitor pregnant patients for destabilization of their heart failure.

Pregnant women with symptomatic cirrhosis generally have poor outcomes including hepatic failure, variceal hemorrhage, pre-term delivery, fetal growth restriction and maternal death. Outcomes are worse with coexisting esophageal varices. Pregnant women with cirrhosis of the liver should be carefully monitored and managed accordingly.

Data

Animal Data

The effects of furosemide on embryonic and fetal development and on pregnant dams were studied in mice, rats and rabbits.

Furosemide caused unexplained maternal deaths and abortions in the rabbit at the lowest dose of 25 mg/kg (approximately 4 times a human i.v. dose of 80 mg based on BSA and oral bioavailability corrections). In another study, a dose of 50 mg/kg (approximately 7 times a human i.v. dose of 80 mg based on BSA and oral bioavailability corrections) also caused maternal deaths and abortions when administered to rabbits between Days 12 and 17 of gestation. In a third study, none of the pregnant rabbits survived an oral dose of 100 mg/kg. Data from the above studies indicate fetal lethality that can precede maternal deaths.

The results of the mouse study and one of the three rabbit studies also showed an increased incidence and severity of hydronephrosis (distention of the renal pelvis and, in some cases, of the ureters) in fetuses of treated dams as compared with the incidence of fetuses from the control group.

8.2 Lactation

Risk Summary

The presence of furosemide has been reported in human milk. There are no data on the effects on the breastfed infant or the effects on milk production. Doses of furosemide associated with clinically significant diuresis may impair milk production. The developmental and health benefits of breastfeeding should be considered along with the mother’s clinical need for furosemide and any potential adverse effects on the breastfed infant from furosemide or from the underlying maternal condition.

8.4 Pediatric Use

Published reports indicate that premature infants with post conceptual age (gestational plus postnatal) less than 31 weeks receiving doses exceeding 1 mg/kg/24 hours may develop plasma levels which could be associated with potential toxic effects including ototoxicity [see Warnings and Precautions (5.3)] .

Furosemide in the first year of life, especially in patients born pre-term, may precipitate nephrocalcinosis/nephrolithiasis [see Warnings and Precautions (5.2)] .

8.5 Geriatric Use

Controlled clinical studies of furosemide did not include sufficient numbers of subjects aged 65 and over to determine whether they respond differently from younger subjects. Other reported clinical experience has not identified differences in responses between the elderly and younger patients. In general, dose selection for the elderly patient should be cautious, usually starting at the low end of the dosing range, reflecting the greater frequency of decreased hepatic, renal or cardiac function, and of concomitant disease or other drug therapy.

This drug is known to be substantially excreted by the kidney, and the risk of toxic reactions to this drug may be greater in patients with impaired renal function. Because elderly patients are more likely to have decreased renal function, care should be taken in dose selection and it may be useful to monitor renal function [see Clinical Pharmacology (12.3)] .

10 OVERDOSAGE

The principal signs and symptoms of overdose with furosemide are dehydration, blood volume reduction, hypotension, electrolyte imbalance, hypokalemia and hypochloremic alkalosis, and are extensions of its diuretic action.

The concentration of furosemide in biological fluids associated with toxicity or death is not known.

Treatment of overdosage is supportive and consists of replacement of excessive fluid and electrolyte losses. Serum electrolytes, carbon dioxide level, and blood pressure should be determined frequently. Adequate drainage must be assured in patients with urinary bladder outlet obstruction (such as prostatic hypertrophy).

Hemodialysis does not accelerate furosemide elimination.

11 DESCRIPTION

Furosemide Injection, USP contains furosemide as the active pharmaceutical ingredient. Furosemide is a loop diuretic which is an anthranilic acid derivative. Furosemide chemical name is 4-chloro- N-furfuryl-5-sulfamoylanthranilic acid.

Furosemide is a white to slightly-yellow crystalline powder. It is practically insoluble in water, sparingly soluble in alcohol, freely soluble in dilute alkali solutions and insoluble in dilute acids.

The structural formula is as follows:

Molecular formula: C12H11CIN2O5S Molecular weight: 330.74

Furosemide Injection, USP 10 mg/mL is a sterile, non-pyrogenic solution, available in single-dose vials for intravenous and intramuscular injection. Each mL contains: Furosemide 10 mg, Sodium Chloride 7.5 mg for isotonicity, Sodium Hydroxide 1.35 mg, Sodium Hydroxide and Hydrochloric Acid, if necessary, to adjust pH between 8.0 and 9.3, Water for Injection q.s.

12 CLINICAL PHARMACOLOGY

12.1 Mechanism of Action

Furosemide inhibits primarily the reabsorption of sodium and chloride not only in the proximal and distal tubules but also in the loop of Henle. The high degree of efficacy is largely due to this unique site of action. The action on the distal tubule is independent of any inhibitory effect on carbonic anhydrase and aldosterone.

12.2 Pharmacodynamics

The onset of diuresis following intravenous administration is within 5 minutes and somewhat later after intramuscular administration. The peak effect occurs within the first half hour. The duration of diuretic effect is approximately 2 hours.

12.3 Pharmacokinetics

Distribution

Furosemide is extensively bound to plasma proteins, mainly to albumin.

Plasma concentrations ranging from 1 to 400 mcg/mL are 91 to 99% bound in healthy individuals. The unbound fraction averages 2.3 to 4.1% at therapeutic concentrations.

Elimination

The terminal half-life of furosemide is approximately 2 hours.

Metabolism

Recent evidence suggests that furosemide glucuronide is the only or at least the major biotransformation product of furosemide in man.

Excretion

Significantly more furosemide is excreted in urine following the intravenous injection than after the tablet or oral solution.

Specific Populations

Geriatric Patients

Furosemide binding to albumin may be reduced in elderly patients. Furosemide is predominantly excreted unchanged in the urine. The renal clearance of furosemide after intravenous administration in older healthy male subjects (60 to 70 years of age) is statistically significantly smaller than in younger healthy male subjects (20 to 35 years of age). The initial diuretic effect of furosemide in older subjects is decreased relative to younger subjects [see Use in Specific Populations (8.5)] .

Pediatric Patients

Based on PK results obtained from 51 premature infants (23-29 weeks gestational age (GA)) receiving repeated doses up to 4 times the maximum recommended total daily dose for intravenous (IV) administration (or 8 times the maximum recommended total daily dose for enteral administration), body weight and postnatal age were found to have an impact on furosemide clearance. Median clearance (normalized by dosing weight) was observed to increase from 8.9 (range: 2.1-21.2) ml/h/kg in infants with postnatal age (PNA) <30 days to 25.3 (range: 8.3 to 44.2) ml/h/kg in infants with PNA >30 days. In addition, higher clearance was observed in infants with higher body weight. Bioavailability of enteral dose compared to IV dose was estimated to be around 79%.

Patients with Renal Impairment

One study in six subjects demonstrated that the combination of furosemide and acetylsalicylic acid temporarily reduced creatinine clearance in patients with chronic renal insufficiency. There are case reports of patients who developed increased BUN, serum creatinine and serum potassium levels, and weight gain when furosemide was used in conjunction with NSAIDs.

13 NONCLINICAL TOXICOLOGY

13.1 Carcinogenesis, Mutagenesis, Impairment of Fertility

Carcinogenesis

Furosemide was tested for carcinogenicity by oral administration in one strain of mice and one strain of rats. A small but significantly increased incidence of mammary gland carcinomas occurred in female mice at a dose approximately 8 times a human i.v. dose of 80 mg based on BSA and oral bioavailability corrections. There were marginal increases in uncommon tumors in male rats at a dose of 15 mg/kg but not at 30 mg/kg.

Mutagenesis

Furosemide was devoid of mutagenic activity in various strains of Salmonella typhimuriumwhen tested in the presence or absence of an in vitrometabolic activation system, and questionably positive for gene mutation in mouse lymphoma cells in the presence of rat liver S9 at the highest dose tested. Furosemide did not induce sister chromatid exchange in human cells in vitro, but other studies on chromosomal aberrations in human cells in vitrogave conflicting results. In Chinese hamster cells it induced chromosomal damage but was questionably positive for sister chromatid exchange. Studies on the induction by furosemide of chromosomal aberrations in mice were inconclusive. The urine of rats treated with this drug did not induce gene conversion in Saccharomyces cerevisiae.

Impairment of Fertility

Furosemide produced no impairment of fertility in male or female rats, at 100 mg/kg/day (the maximum effective diuretic dose in the rat), approximately 7 times a human i.v. dose of 80 mg based on BSA and oral bioavailability corrections.

16 HOW SUPPLIED/STORAGE AND HANDLING

Furosemide Injection is a sterile, colorless solution for injection, available as a single-dose vial that contains 10 mg/mL of furosemide, and is supplied as follows:

Unit of Sale | Presentations | Strength
NDC 0143-9155-25 | Box of 25 amber glass single-dose vials | 20 mg/2 mL; (10 mg/mL)
NDC 0143-9156-10 | Box of 10 amber glass single-dose vials | 40 mg/4 mL; (10 mg/mL)
NDC 0143-9157-10 | Box of 10 amber glass single-dose vials | 100 mg/10 mL; (10 mg/mL)
NDC 0143-9158-01 | Box of 1 clear glass single-dose vial with hanger | 500 mg/50 mL; (10 mg/mL)
NDC 0143-9159-01 | Box of 1 clear glass single-dose vial with hanger | 1,000 mg/100 mL; (10 mg/mL)

Discard unused portion. Do not use if solution is discolored or contains particulate.

2 mL, 4 mL and 10 mL amber glass single-dose vials:

Store at room temperature 20°C to 25°C (68°F to 77°F); excursions permitted between 15°C and 30°C (59°F and 86°F). [See USP Controlled Room Temperature]. Protect from light.

50 mL and 100 mL clear glass single-dose vials:

Store at room temperature 20°C to 25°C (68°F to 77°F); excursions permitted between 15°C and 30°C (59°F and 86°F). [See USP Controlled Room Temperature]. Protect from light. Retain in carton until contents are used.

17 PATIENT COUNSELING INFORMATION

Fluid, Electrolyte, and Metabolic Abnormalities

Advise patients that they may experience symptoms from excessive fluid and/or electrolyte losses. The postural hypotension that sometimes occurs can usually be managed by getting up slowly. Potassium supplements and/or dietary measures may be needed to control or avoid hypokalemia [see Warnings and Precautions (5.1)] .

Advise patients that furosemide may increase blood glucose levels and thereby affect urine glucose tests [see Warnings and Precautions (5.1)] .

Photosensitivity

The skin of some patients may be more sensitive to the effects of sunlight while taking furosemide [see Adverse Reactions (6)] .

Advise hypertensive patients to avoid medications that may increase blood pressure, including over-the-counter products for appetite suppression and cold symptoms [see Drug Interactions (7.1)] .

This product’s labeling may have been updated. For the most recent prescribing information, please visit www.hikma.com.

Manufactured by:HIKMA FARMACÊUTICA (PORTUGAL), S.A.

Estrada do Rio da Mό, 8, 8A e 8B – Fervença – 2705-906 Terrugem SNT, PORTUGAL

Distributed by:Hikma Pharmaceuticals USA Inc.

Berkeley Heights, NJ 07922

March 2025 PIN347-WES/5

PRINCIPAL DISPLAY PANEL - VIAL LABEL

Furosemide Injection, USP

100 mg/10 mL (10 mg/mL)

10 mL Single-Dose Vial

For Intravenous or Intramuscular Use

Discard unused portion

Rx Only

PRINCIPAL DISPLAY PANEL - OUTER PACKAGE

NDC 71872-7350-1

Furosemide Injection, USP

100 mg/10 mL (10 mg/mL)

1 x 10 mL Single-Dose Vial

For Intravenous or Intramuscular Use

Discard unused portion

Rx Only